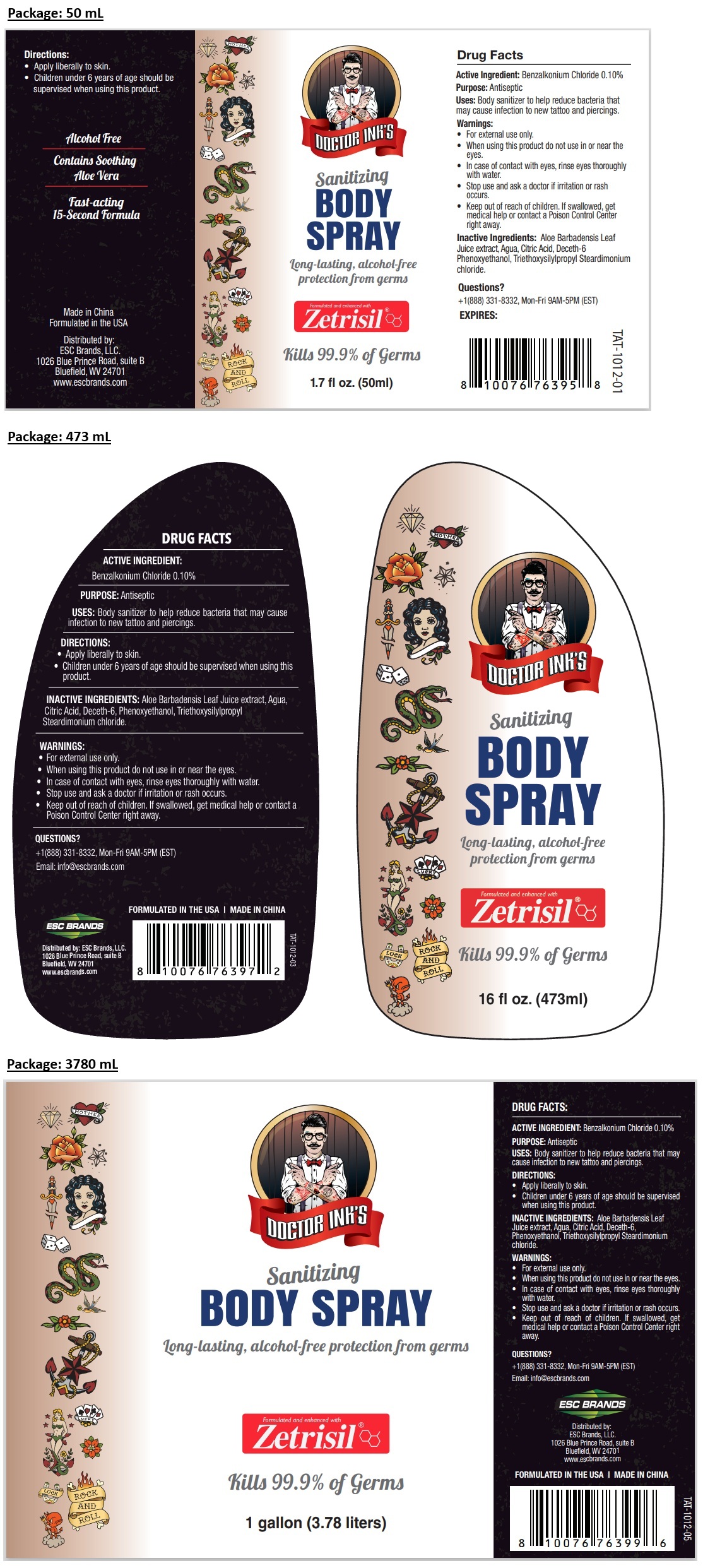 DRUG LABEL: DOCTOR INKS Sanitizing BODY
NDC: 71884-202 | Form: SPRAY
Manufacturer: Enviro Specialty Chemicals Inc
Category: otc | Type: HUMAN OTC DRUG LABEL
Date: 20260123

ACTIVE INGREDIENTS: BENZALKONIUM CHLORIDE 1 mg/1 mL
INACTIVE INGREDIENTS: ALOE VERA LEAF; WATER; CITRIC ACID MONOHYDRATE; DECETH-6; PHENOXYETHANOL; TRIETHOXYSILYLPROPYL STEARDIMONIUM CHLORIDE

DOCTOR INK'S Sanitizing BODY SPRAY

ACTIVE INGREDIENT:

Benzalkonium Chloride 0.10%

PURPOSE:

Antiseptic

USES:

Body sanitizer to help reduce bacteria that may cause infection to new tattoo and piercings.

DIRECTIONS:

• Apply liberally to skin.
• Children under 6 years of age should be supervised when using this product.

INACTIVE INGREDIENTS

Aloe Barbadensis Leaf Juice Extract, Agua, Citric Acid, Deceth-6, Phenoxyethanol, Triethoxysilylpropyl Steardimonium chloride.

WARNINGS:

• For external use only.
• When using this product do not use in or near the eyes.
• In case of contact with eyes, rinse eyes thoroughly with water.
• Stop use and ask a doctor if irritation or rash occurs.

Keep out of reach of children. If swallowed, get medical help or contact a Poison Control Center right away.

QUESTIONS:

+1(888) 331-8332, Mon-Fri 9AM-5PM (EST)
Email: info@escbrands.com

Long-lasting, alcohol-free
protection from germs

Formulated and enhanced with Zetrisil®

Kills 99.9% of Germs

Alcohol Free

Contains Soothing Aloe Vera

Fast-acting 15-Second Formula

Distributed by:
ESC Brands, LLC.
1026 Blue Prince Road, suite B
Bluefield, WV 24701
www.escbrands.com

FORMULATED IN THE USA | MADE IN CHINA